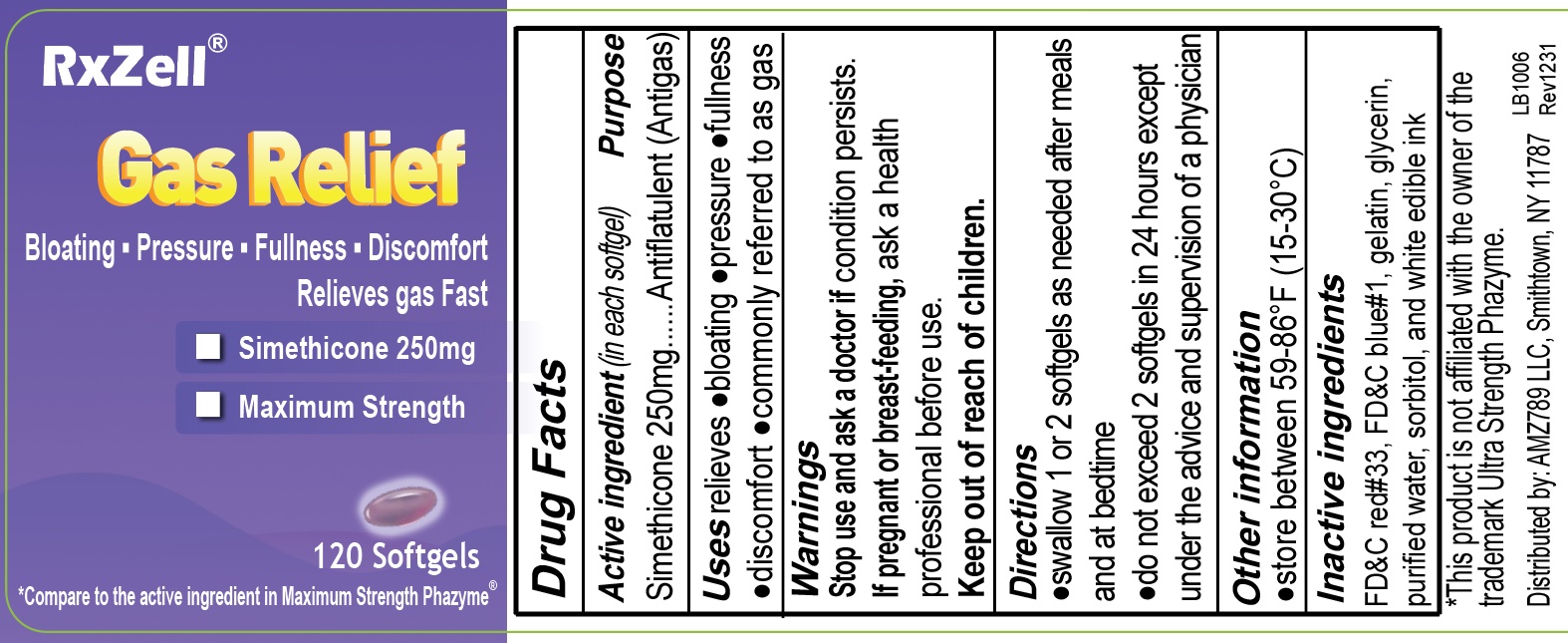 DRUG LABEL: Simethicone 250mg
NDC: 73629-006 | Form: CAPSULE, LIQUID FILLED
Manufacturer: AMZ789 LLC
Category: otc | Type: HUMAN OTC DRUG LABEL
Date: 20250108

ACTIVE INGREDIENTS: DIMETHICONE 250 mg/1 1
INACTIVE INGREDIENTS: FD&C BLUE NO. 1; GELATIN; FD&C RED NO. 40; GLYCERIN; WATER

Simethicone 250mg

ACTIVE INGREDIENT

Simethicone 180mg

PURPOSE

relieves bloating, pressure, fullness, commonly referred to as gas

WARNINGS

stop use and ask a doctor if condition persists

PREGNANCY OR BREAST FEEDING

if pregnant or breast-feedingm ask a health professional before use

Keep out of reach of children

DOSAGE AND ADMINISTRATION

▪ swallow one or two softgels as needed after a meal

▪ do not exceed two softgels per day except under the advice and supervision of a physician

INDICATIONS AND USAGE

Uses relieves ▪ bloating ▪ pressure ▪ fullness commonly referred to as gas

INACTIVE INGREDIENT

FD&C Blue #1, FD&C Red #40, gelatin, glycerin, purified water, and white edible ink